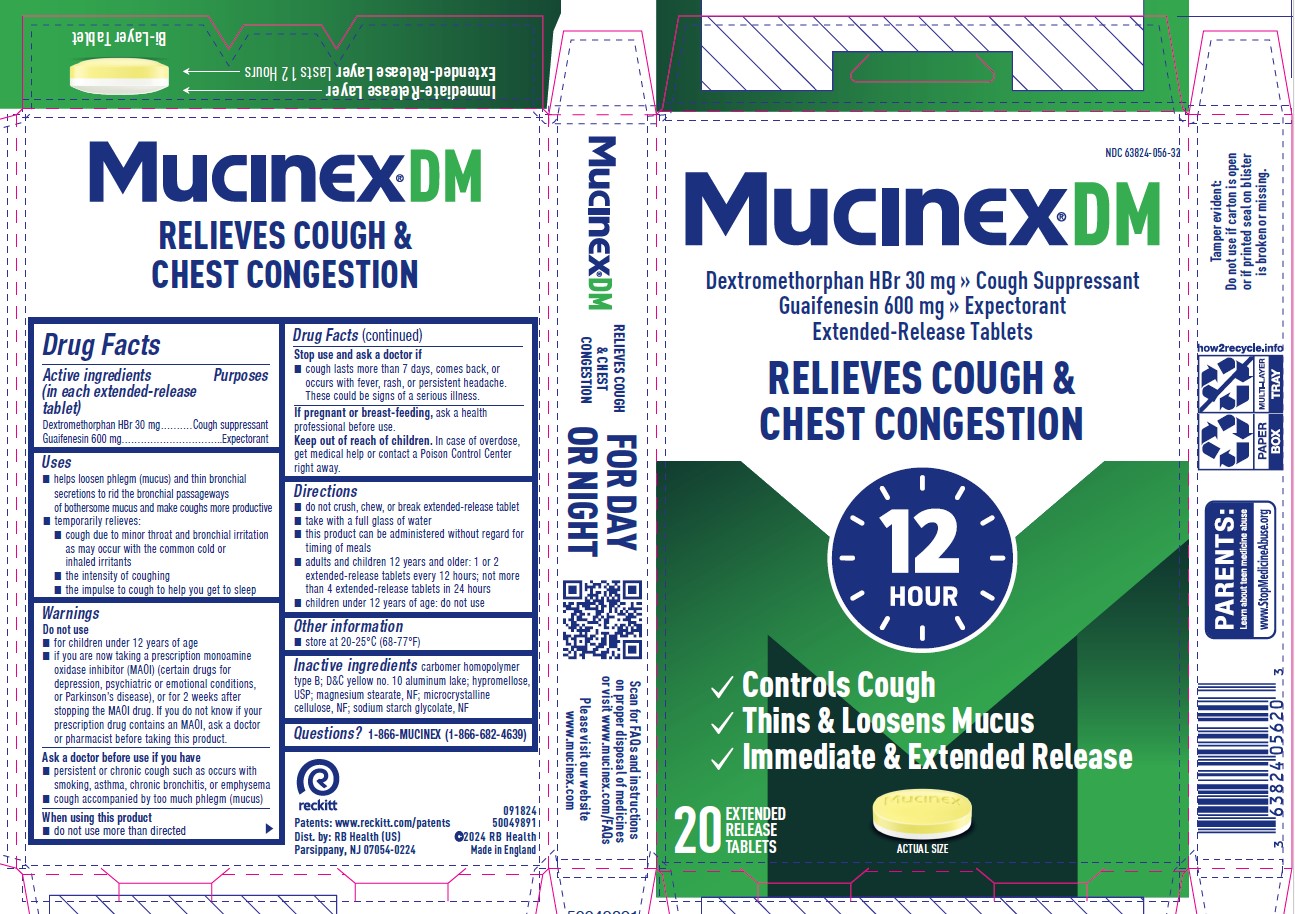 DRUG LABEL: Mucinex DM
NDC: 85237-1650 | Form: TABLET, EXTENDED RELEASE
Manufacturer: Select Consumer Group
Category: otc | Type: HUMAN OTC DRUG LABEL
Date: 20251228

ACTIVE INGREDIENTS: GUAIFENESIN 600 mg/1 1; DEXTROMETHORPHAN HYDROBROMIDE 30 mg/1 1
INACTIVE INGREDIENTS: CARBOMER HOMOPOLYMER TYPE B (ALLYL PENTAERYTHRITOL CROSSLINKED); D&C YELLOW NO. 10; ALUMINUM OXIDE; HYPROMELLOSE, UNSPECIFIED; MAGNESIUM STEARATE; MICROCRYSTALLINE CELLULOSE

Mucinex®DM

Drug Facts

Active ingredients (in each extended-release tablet)
Dextromethorphan HBr 30 mg
Guaifenesin 600 mg

PURPOSE

Active ingredients (in each extended-release tablet) | Purposes
Dextromethorphan HBr 30 mg | Cough suppressant
Guaifenesin 600 mg | Expectorant

Uses

- helps loosen phlegm (mucus) and thin bronchial secretions to rid the bronchial passageways of bothersome mucus and make coughs more productive
- temporarily relieves:
  - cough due to minor throat and bronchial irritation as may occur with the common cold or inhaled irritants
  - the intensity of coughing
  - the impulse to cough to help you get to sleep

Warnings

Do not use

- for children under 12 years of age
- if you are now taking a prescription monoamine oxidase inhibitor (MAOI) (certain drugs for depression, psychiatric or emotional conditions, or Parkinson's disease), or for 2 weeks after stopping the MAOI drug. If you do not know if your prescription drug contains an MAOI, ask a doctor or pharmacist before taking this product.

Ask a doctor before use if you have

- persistent or chronic cough such as occurs with smoking, asthma, chronic bronchitis, or emphysema
- cough accompanied by too much phlegm (mucus)

When using this product

- do not use more than directed

Stop use and ask a doctor if

- cough lasts more than 7 days, comes back, or occurs with fever, rash, or persistent headache. These could be signs of a serious illness.

PREGNANCY OR BREAST FEEDING

If pregnant or breast-feeding,ask a health professional before use.

Keep out of reach of children.In case of overdose, get medical help or contact a Poison Control Center right away.

Directions

- do not crush, chew, or break extended-release tablet
- take with a full glass of water
- this product can be administered without regard for timing of meals
- adults and children 12 years and older: 1 or 2 extended-release tablets every 12 hours; not more than 4 extended-release tablets in 24 hours
- children under 12 years of age: do not use

Other information

- store at 20-25°C (68-77°F)

Inactive ingredients

carbomer homopolymer type B; D&C yellow no. 10 aluminum lake; hypromellose, USP; magnesium stearate, NF; microcrystalline cellulose, NF; sodium starch glycolate, NF

Questions?

1-866-MUCINEX (1-866-682-4639)

Dist. by: RB Health (US)
Parsippany, NJ 07054-0224

Made in England

PRINCIPAL DISPLAY PANEL - 20 Tablet Blister Pack Carton

NDC 63824-056-32

Mucinex®DM

600 mg guaifenesin & 30 mg dextromethorphan HBr
extended-release tablets

EXPECTORANT & COUGH SUPPRESSANT

12
HOUR®

- Controls Cough
- Thins and Loosens Mucus
- Immediate and Extended Release

20
EXTENDED-RELEASE TABLETS